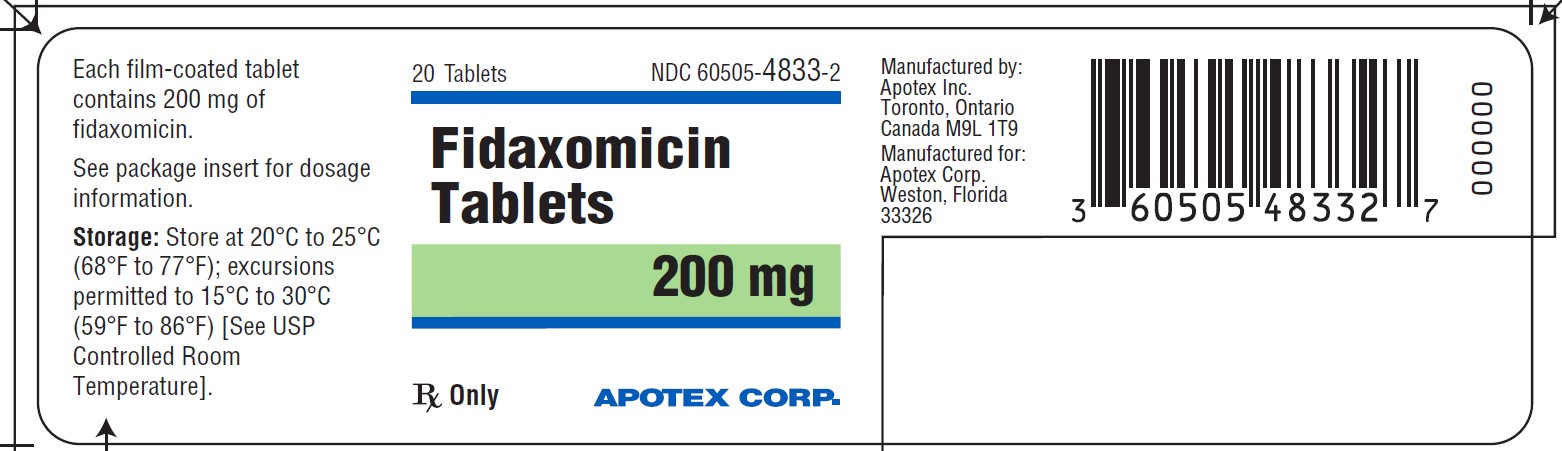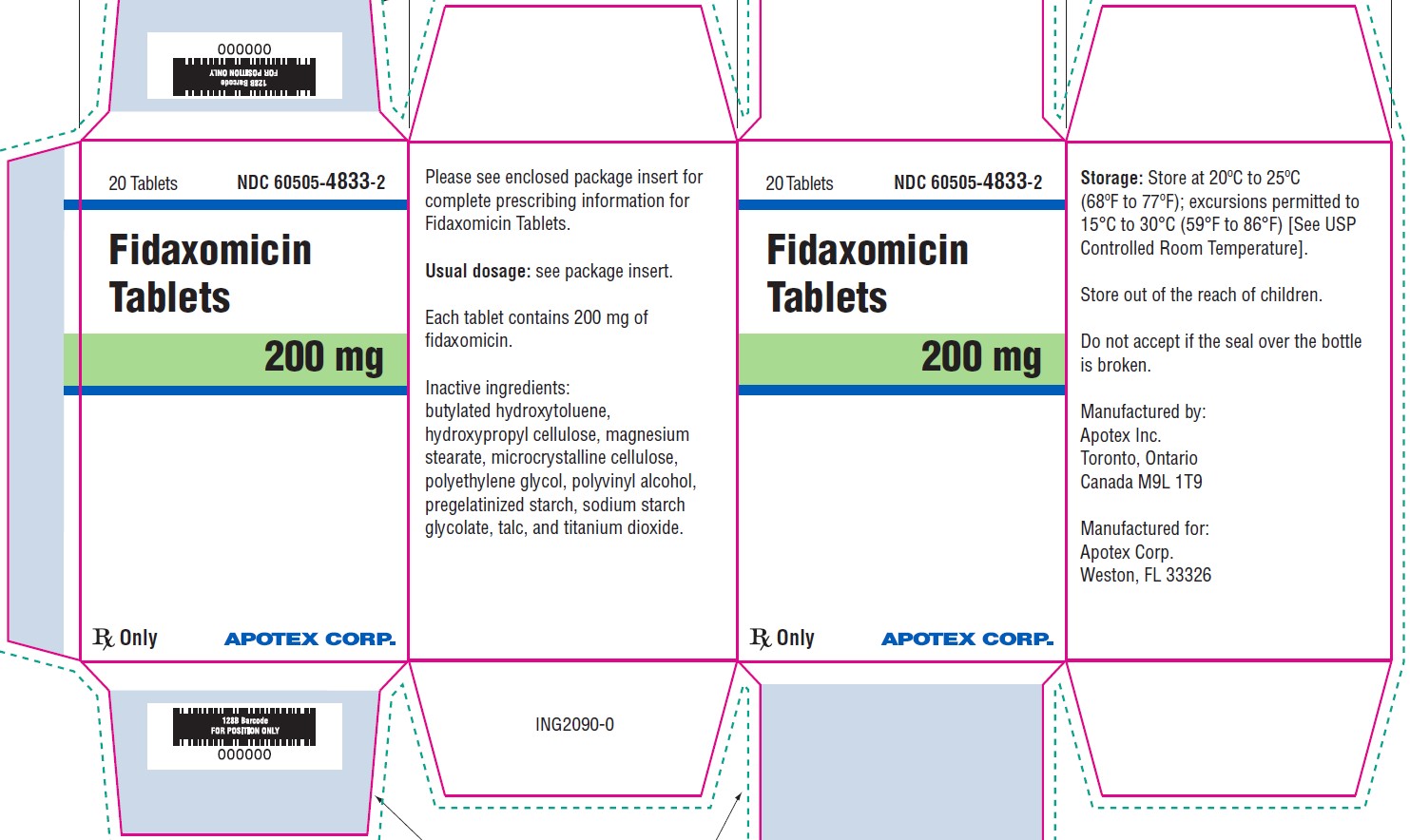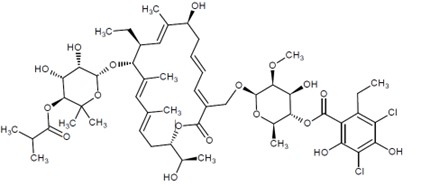 DRUG LABEL: Fidaxomicin
NDC: 60505-4833 | Form: TABLET, FILM COATED
Manufacturer: Apotex Corp.
Category: prescription | Type: HUMAN PRESCRIPTION DRUG LABEL
Date: 20260213

ACTIVE INGREDIENTS: Fidaxomicin 200 mg/1 1
INACTIVE INGREDIENTS: Butylated Hydroxytoluene; Hydroxypropyl Cellulose (1600000 WAMW); Magnesium Stearate; MICROCRYSTALLINE CELLULOSE; Polyethylene Glycol 8000; POLYVINYL ALCOHOL, UNSPECIFIED; Starch, Corn; Sodium Starch Glycolate Type A Potato; Talc; Titanium Dioxide

HIGHLIGHTS OF PRESCRIBING INFORMATION

These highlights do not include all the information needed to use FIDAXOMICIN TABLETS safely and effectively. See full prescribing information for FIDAXOMICIN TABLETS.
FIDAXOMICIN tablets, for oral use
Initial U.S. Approval: 2011

1 INDICATIONS AND USAGE

Fidaxomicin tablets are a macrolide antibacterial indicated in adult patients for the treatment of C. difficile-associated diarrhea. (1.1)

To reduce the development of drug-resistant bacteria and maintain the effectiveness of fidaxomicin tablets and other antibacterial drugs, fidaxomicin tablets should be used only to treat infections that are proven or strongly suspected to be caused by C. difficile. (1.2)

2 DOSAGE AND ADMINISTRATION

- Fidaxomicin tablets are administered orally with or without food. (2.1)
- Adults
  - One 200 mg tablet orally twice daily for 10 days. (2.2)

3 DOSAGE FORMS AND STRENGTHS

- Film-coated tablets: 200 mg (3)

4 CONTRAINDICATIONS

Fidaxomicin tablets are contraindicated in patients who have known hypersensitivity to fidaxomicin or any other ingredient in fidaxomicin tablets. (4)

5 WARNINGS AND PRECAUTIONS

- Acute hypersensitivity reactions (angioedema, dyspnea, pruritus, and rash) have been reported. If a severe hypersensitivity reaction occurs, discontinue fidaxomicin tablets. (5.1)
- Fidaxomicin tablets is not expected to be effective for the treatment of other types of infections due to minimal systemic absorption of fidaxomicin. Fidaxomicin tablets should only be used for the treatment of C. difficile-associated diarrhea. (5.2)
- Development of drug-resistant bacteria: Only use fidaxomicin tablets for infection proven or strongly suspected to be caused by C. difficile. (5.3)

6 ADVERSE REACTIONS

The most common adverse reactions in adults (incidence ≥2%) are nausea, vomiting, abdominal pain, gastrointestinal hemorrhage, anemia, and neutropenia. (6)

To report SUSPECTED ADVERSE REACTIONS, contact Apotex Corp., at 1-800-706-5575 or FDA at 1-800-FDA-1088 or www.fda.gov/medwatch.

8 USE IN SPECIFIC POPULATIONS

Pediatrics: The safety and effectiveness of fidaxomicin tablets have not been established in pediatric patients younger than 6 months of age. (8.4)

Pediatric use information is approved for Cubist Pharmaceuticals LLC's DIFICID® (fidaxomicin) tablets. However, due to Cubist Pharmaceuticals LLC's marketing exclusivity rights, this drug product is not labeled with that information.

FULL PRESCRIBING INFORMATION

1 INDICATIONS AND USAGE

1.1 Clostridioides difficile-Associated Diarrhea

Fidaxomicin tablets are indicated in adult patients for the treatment of C. difficile-associated diarrhea (CDAD).

1.2 Usage

To reduce the development of drug-resistant bacteria and maintain the effectiveness of fidaxomicin tablets and other antibacterial drugs, fidaxomicin tablets should be used only to treat infections that are proven or strongly suspected to be caused by C. difficile. When culture and susceptibility information are available, they should be considered in selecting or modifying antibacterial therapy. In the absence of such data, local epidemiology and susceptibility patterns may contribute to the empiric selection of therapy.

Pediatric use information is approved for Cubist Pharmaceuticals LLC's DIFICID® (fidaxomicin) tablets. However, due to Cubist Pharmaceuticals LLC's marketing exclusivity rights, this drug product is not labeled with that information.

2 DOSAGE AND ADMINISTRATION

2.1 Important Administration Instructions

Fidaxomicin tablets are available for oral administration as 200 mg tablets. Fidaxomicin tablets are administered orally with or without food.

2.2 Adult Patients

The recommended dosage for adults is one 200 mg fidaxomicin tablet orally twice daily for 10 days.

Pediatric use information is approved for Cubist Pharmaceuticals LLC's DIFICID® (fidaxomicin) tablets. However, due to Cubist Pharmaceuticals LLC's marketing exclusivity rights, this drug product is not labeled with that information.

3 DOSAGE FORMS AND STRENGTHS

200 mg white to off-white, capsule shape, biconvex film-coated tablet. Engraved “F200” on one side, “APO” on the other side.

4 CONTRAINDICATIONS

Fidaxomicin tablets are contraindicated in patients who have known hypersensitivity to fidaxomicin or any other ingredient in fidaxomicin tablets [see Warnings and Precautions (5.1)].

5 WARNINGS AND PRECAUTIONS

5.1 Hypersensitivity Reactions

Acute hypersensitivity reactions, including dyspnea, rash, pruritus, and angioedema of the mouth, throat, and face have been reported with fidaxomicin tablets. If a severe hypersensitivity reaction occurs, fidaxomicin tablets should be discontinued and appropriate therapy should be instituted.

Some patients with hypersensitivity reactions to fidaxomicin tablets also reported a history of allergy to other macrolides. Physicians prescribing fidaxomicin tablets to patients with a known macrolide allergy should be aware of the possibility of hypersensitivity reactions.

5.2 Not for Use in Infections Other than C. difficile-Associated Diarrhea

Fidaxomicin tablets are not expected to be effective for the treatment of other types of infections due to minimal systemic absorption of fidaxomicin [see Clinical Pharmacology (12.3)]. Fidaxomicin tablets have not been studied for the treatment of infections other than CDAD. Fidaxomicin tablets should only be used for the treatment of CDAD.

5.3 Development of Drug-Resistant Bacteria

Prescribing fidaxomicin tablets in the absence of proven or strongly suspected C. difficile infection is unlikely to provide benefit to the patient and increases the risk of the development of drug-resistant bacteria.

6 ADVERSE REACTIONS

6.1 Clinical Trials Experience

Because clinical trials are conducted under widely varying conditions, adverse reaction rates observed in the clinical trials of a drug cannot be directly compared to rates in the clinical trials of another drug and may not reflect the rates observed in practice.

Adults

The safety of fidaxomicin 200 mg tablets taken twice a day for 10 days was evaluated in 564 adult patients with CDAD in two active-controlled trials with 86.7% of patients receiving a full course of treatment.

Thirty-three adult patients receiving fidaxomicin tablets (5.9%) withdrew from trials as a result of adverse reactions (AR). The types of AR resulting in withdrawal from the study varied considerably. Vomiting was the primary adverse reaction leading to discontinuation of dosing; this occurred at an incidence of 0.5% in both the fidaxomicin tablets and vancomycin patients in Phase 3 trials. The most common selected adverse reactions occurring in ≥2% of adult patients treated with fidaxomicin tablets are listed in Table 2.

Table 2: Selected Adverse Reactions with an Incidence of ≥2% Reported in Fidaxomicin-Treated Adult Patients in Controlled Trials

System Organ Class Adverse Reaction | Fidaxomicin (N=564) | Vancomycin (N=583)
System Organ Class Adverse Reaction | n (%) | n (%)
Blood and Lymphatic System Disorders
Anemia | 14 (2%) | 12 (2%)
Neutropenia | 14 (2%) | 6 (1%)
Gastrointestinal Disorders
Nausea | 62 (11%) | 66 (11%)
Vomiting | 41 (7%) | 37 (6%)
Abdominal Pain | 33 (6%) | 23 (4%)
Gastrointestinal Hemorrhage | 20 (4%) | 12 (2%)

The following adverse reactions were reported in <2% of adult patients taking fidaxomicin tablets in controlled trials:

Gastrointestinal Disorders: abdominal distension, abdominal tenderness, dyspepsia, dysphagia, flatulence, intestinal obstruction, megacolon

Investigations: increased blood alkaline phosphatase, decreased blood bicarbonate, increased hepatic enzymes, decreased platelet count

Metabolism and Nutrition Disorders: hyperglycemia, metabolic acidosis

Skin and Subcutaneous Tissue Disorders: drug eruption, pruritus, rash

6.2 Post Marketing Experience

The following adverse reactions have been identified during post-approval use of fidaxomicin tablets. Because these reactions are reported voluntarily from a population of uncertain size, it is not always possible to reliably estimate their frequency or establish a causal relationship to drug exposure.

Hypersensitivity reactions (dyspnea, angioedema, rash, pruritus)

Pediatric use information is approved for Cubist Pharmaceuticals LLC's DIFICID® (fidaxomicin) tablets. However, due to Cubist Pharmaceuticals LLC's marketing exclusivity rights, this drug product is not labeled with that information.

7 DRUG INTERACTIONS

Fidaxomicin and its main metabolite, OP-1118, are substrates of the efflux transporter, P-glycoprotein (P-gp), which is expressed in the gastrointestinal tract.

7.1 Cyclosporine

Cyclosporine is an inhibitor of multiple transporters, including P-gp. When cyclosporine was co-administered with fidaxomicin tablets, plasma concentrations of fidaxomicin and OP-1118 were significantly increased but remained in the ng/mL range [see Clinical Pharmacology (12.3)]. Concentrations of fidaxomicin and OP-1118 may also be decreased at the site of action (i.e., gastrointestinal tract) via P-gp inhibition; however, concomitant P-gp inhibitor use had no attributable effect on safety or treatment outcome of fidaxomicin-treated adult patients in controlled clinical trials. Based on these results, fidaxomicin may be co-administered with P-gp inhibitors and no dose adjustment is recommended.

8 USE IN SPECIFIC POPULATIONS

8.1 Pregnancy

Risk Summary

The limited available data on use of fidaxomicin tablets in pregnant women are insufficient to inform any drug-associated risk for major birth defects, miscarriage or adverse maternal or fetal outcomes. Embryo-fetal reproduction studies in rats and rabbits dosed intravenously during organogenesis revealed no evidence of harm to the fetus at fidaxomicin and OP-1118 (its main metabolite) exposures 65-fold or higher than the clinical exposure at the fidaxomicin tablets recommended dose [see Data].

The estimated background risk of major birth defects and miscarriage for the indicated populations is unknown. All pregnancies have a background risk of birth defect, loss, or other adverse outcomes. In the U.S. general population, the estimated background risk of major birth defects and miscarriage in clinically recognized pregnancies is 2 to 4% and 15 to 20%, respectively.

Data

Animal Data

In pregnant rats, fidaxomicin was administered intravenously at doses of 4, 8, and 15 mg/kg/day from gestation day 6 through 17 (during the period of organogenesis). No embryo/fetal effects were noted in this study at exposures (AUC) 193-fold higher for fidaxomicin, and 65-fold higher for OP-1118 than the clinical exposure at the fidaxomicin tablets recommended dose.

In pregnant rabbits, fidaxomicin was administered intravenously at doses of 2, 4, and 7.5 mg/kg/day from gestation day 6 through 18 (during the period of organogenesis). No embryo/fetal effects were noted in this study at exposures 66-fold higher for fidaxomicin, and 245-fold higher for OP-1118 than the clinical exposure at the fidaxomicin tablets recommended dose.

8.2 Lactation

Risk Summary

There is no information on the presence of fidaxomicin or its main metabolite, OP-1118, in human milk, the effects on the breastfed infant, or the effects on milk production. The developmental and health benefits of breastfeeding should be considered along with the mother’s clinical need for fidaxomicin tablets and any potential adverse effects on the breastfed infant from fidaxomicin tablets or from the underlying maternal condition.

8.4 Pediatric Use

The safety and effectiveness of fidaxomicin tablets have not been established in pediatric patients younger than 6 months of age.

Pediatric use information is approved for Cubist Pharmaceuticals LLC's DIFICID® (fidaxomicin) tablets. However, due to Cubist Pharmaceuticals LLC's marketing exclusivity rights, this drug product is not labeled with that information.

8.5 Geriatric Use

Of the total number of patients in controlled trials of fidaxomicin tablets, 50% were 65 years of age and over, while 31% were 75 and over. No overall differences in safety or effectiveness of fidaxomicin tablets compared to vancomycin were observed between these subjects and younger subjects.

In controlled trials, elderly patients (≥65 years of age) had higher plasma concentrations of fidaxomicin and its main metabolite, OP-1118, versus non-elderly patients (<65 years of age) [see Clinical Pharmacology (12.3)]. However, greater exposures in elderly patients were not considered to be clinically significant. No dose adjustment is recommended for elderly patients.

10 OVERDOSAGE

No cases of acute overdose have been reported in humans. No drug-related adverse effects were seen in dogs dosed with fidaxomicin tablets at 9,600 mg/day (over 100 times the human dose, scaled by weight) for 3 months.

11 DESCRIPTION

Fidaxomicin tablets (fidaxomicin) is a macrolide antibacterial drug for oral administration. Its CAS chemical name is Oxacyclooctadeca-3,5,9,13,15-pentaen-2-one, 3-[[[6-deoxy-4-O-(3,5-dichloro-2-ethyl-4,6-dihydroxybenzoyl)-2-O-methyl-β-D-mannopyranosyl]oxy]methyl]-12-[[6-deoxy-5-C-methyl-4-O-(2-methyl-1-oxopropyl)-β-D-lyxo-hexopyranosyl]oxy]-11-ethyl-8-hydroxy-18-[(1R)-1-hydroxyethyl]-9,13,15-trimethyl-,(3E,5E,8S,9E,11S,12R,13E,15E,18S)-.The structural formula of fidaxomicin is shown in Figure 1.

Figure 1: Structural Formula of Fidaxomicin

Fidaxomicin tablets are film-coated and contain 200 mg of fidaxomicin per tablet and the following inactive ingredients: butylated hydroxytoluene, hydroxypropyl cellulose, magnesium stearate, microcrystalline cellulose, polyethylene glycol, polyvinyl alcohol, pregelatinized starch, sodium starch glycolate, talc, and titanium dioxide.

12 CLINICAL PHARMACOLOGY

12.1 Mechanism of Action

Fidaxomicin is an antibacterial drug [see Microbiology (12.4)].

12.2 Pharmacodynamics

Fidaxomicin acts locally in the gastrointestinal tract on C. difficile. In a dose-ranging trial (N=48) of fidaxomicin using 50 mg, 100 mg, and 200 mg twice daily for 10 days, a dose-response relationship was observed for efficacy.

12.3 Pharmacokinetics

The pharmacokinetic parameters of fidaxomicin and its main metabolite OP-1118 following a single dose of 200 mg in healthy adult males (N=14) are summarized in Table 4.

Table 4: Mean (± Standard Deviation) Pharmacokinetic Parameters of Fidaxomicin 200 mg in Healthy Adult Males

Parameter | Fidaxomicin |  | OP-1118
Parameter | N | Value | N | Value
Cmax (ng/mL) | 14 | 5.20 ± 2.81 | 14 | 12.0 ± 6.06
Tmax (h)* | 14 | 2.00 (1.00-5.00) | 14 | 1.02 (1.00-5.00)
AUC0-t (ng-h/mL) | 14 | 48.3 ± 18.4 | 14 | 103 ± 39.4
AUC 0-∞ (ng-h/mL) | 9 | 62.9 ± 19.5 | 10 | 118 ± 43.3
t1/2 (h) | 9 | 11.7 ± 4.80 | 10 | 11.2 ± 3.01

* Tmax, reported as median (range).

Cmax, maximum observed concentration; Tmax, time to maximum observed concentration; AUC0-t, area under the concentration-time curve from time 0 to the last measured concentration; AUC0-∞, area under the concentration-time curve from time 0 to infinity; t1/2, elimination half-life

Absorption

Fidaxomicin has minimal systemic absorption following oral administration, with plasma concentrations of fidaxomicin and OP-1118 in the ng/mL range at the therapeutic dose. In fidaxomicin-treated patients from controlled trials, plasma concentrations of fidaxomicin and OP-1118 obtained within the Tmax window (1 to 5 hours) were approximately 2- to 6-fold higher than Cmax values in healthy adults. Following administration of fidaxomicin tablets 200 mg twice daily for 10 days, OP-1118 plasma concentrations within the Tmax window were approximately 50%-80% higher than on Day 1, while concentrations of fidaxomicin were similar on Days 1 and 10.

In a food-effect study involving administration of fidaxomicin tablets to healthy adults (N=28) with a high-fat meal versus under fasting conditions, Cmax of fidaxomicin and OP-1118 decreased by 21.5% and 33.4%, respectively, while AUC0-t remained unchanged. This decrease in Cmax is not considered clinically significant, and thus, fidaxomicin tablets may be administered with or without food.

Distribution

Fidaxomicin is mainly confined to the gastrointestinal tract following oral administration. In selected patients (N=8) treated with fidaxomicin tablets 200 mg twice daily for 10 days from controlled trials, fecal concentrations of fidaxomicin and OP-1118 obtained within 24 hours of the last dose ranged from 639 to 2,710 mcg /g and 213 to 1,210 mcg/g, respectively. In contrast, plasma concentrations of fidaxomicin and OP-1118 within the Tmax window (1 to 5 hours) ranged 2 to 179 ng/mL and 10 to 829 ng/mL, respectively.

Elimination

Metabolism

Fidaxomicin is primarily transformed by hydrolysis at the isobutyryl ester to form its main and microbiologically active metabolite, OP-1118. Metabolism of fidaxomicin and formation of OP-1118 are not dependent on cytochrome P450 (CYP) enzymes.

At the therapeutic dose, OP-1118 was the predominant circulating compound in healthy adults, followed by fidaxomicin.

Excretion

Fidaxomicin is mainly excreted in feces. In one trial of healthy adults (N=11), more than 92% of the dose was recovered in the stool as fidaxomicin and OP-1118 following single doses of 200 mg and 300 mg. In another trial of healthy adults (N=6), 0.59% of the dose was recovered in urine as OP-1118 only following a single dose of 200 mg.

Specific Populations

Geriatric Patients

In controlled trials of patients treated with fidaxomicin tablets 200 mg twice daily for 10 days, mean and median values of fidaxomicin and OP-1118 plasma concentrations within the Tmax window (1 to 5 hours) were approximately 2- to 4-fold higher in elderly patients (≥65 years of age) versus non-elderly patients (<65 years of age). Despite greater exposures in elderly patients, fidaxomicin and OP-1118 plasma concentrations remained in the ng/mL range [see Use in Specific Populations (8.5)].

Pediatric Patients

Pediatric use information is approved for Cubist Pharmaceuticals LLC's DIFICID® (fidaxomicin) tablets. However, due to Cubist Pharmaceuticals LLC's marketing exclusivity rights, this drug product is not labeled with that information.

Male and Female Patients

Plasma concentrations of fidaxomicin and OP-1118 within the Tmax window (1 to 5 hours) did not vary by gender in patients treated with fidaxomicin tablets 200 mg twice daily for 10 days from controlled trials. No dose adjustment is recommended based on gender.

Patients with Renal Impairment

In controlled trials of patients treated with fidaxomicin tablets 200 mg twice daily for 10 days, plasma concentrations of fidaxomicin and OP-1118 within the Tmax window (1 to 5 hours) did not vary by severity of renal impairment (based on creatinine clearance) between mild (51 to 79 mL/min), moderate (31 to 50 mL/min), and severe (≤ 30 mL/min) categories. No dose adjustment is recommended based on renal function.

Patients with Hepatic Impairment

The impact of hepatic impairment on the pharmacokinetics of fidaxomicin has not been evaluated. Because fidaxomicin and OP-1118 do not appear to undergo significant hepatic metabolism, elimination of fidaxomicin and OP-1118 is not expected to be significantly affected by hepatic impairment.

Drug Interaction Studies

In vivo studies were conducted to evaluate intestinal drug-drug interactions of fidaxomicin as a P-gp substrate, P-gp inhibitor, and inhibitor of major CYP enzymes expressed in the gastrointestinal tract (CYP3A4, CYP2C9, and CYP2C19).

Table 5 summarizes the impact of a co-administered drug (P-gp inhibitor) on the pharmacokinetics of fidaxomicin [see Drug Interactions (7.1)].

Table 5: Pharmacokinetic Parameters of Fidaxomicin and OP-1118 in the Presence of a Co-Administered Drug

Parameter | Cyclosporine 200 mg + Fidaxomicin 200 mg* (N=14) |  | Fidaxomicin 200 mg Alone (N=14) |  | Mean Ratio of Parameters With/Without Co- Administered Drug (90% CI †) No Effect = 1.00
Parameter | N | Mean | N | Mean | Mean Ratio of Parameters With/Without Co- Administered Drug (90% CI †) No Effect = 1.00
Fidaxomicin
Cmax (ng/mL) | 14 | 19.4 | 14 | 4.67 | 4.15 (3.23-5.32)
AUC0-∞ (ng-h/mL) | 8 | 114 | 9 | 59.5 | 1.92 (1.39-2.64)
OP-1118
Cmax (ng/mL) | 14 | 100 | 14 | 10.6 | 9.51 (6.93-13.05)
AUC0-∞ (ng-h/mL) | 12 | 438 | 10 | 106 | 4.11 (3.06-5.53)

* Cyclosporine was administered 1 hour before fidaxomicin.

† CI - confidence interval

Fidaxomicin had no significant impact on the pharmacokinetics of the following co-administered drugs: digoxin (P-gp substrate), midazolam (CYP3A4 substrate), warfarin (CYP2C9 substrate), and omeprazole (CYP2C19 substrate). No dose adjustment is warranted when fidaxomicin is co-administered with substrates of P-gp or CYP enzymes.

12.4 Microbiology

Mechanism of Action

Fidaxomicin is a fermentation product obtained from the Actinomycete Dactylosporangium aurantiacum. Fidaxomicin is a macrolide antibacterial drug that inhibits RNA synthesis by binding to RNA polymerases. Fidaxomicin is bactericidal against C. difficile in vitro, and demonstrates a post-antibiotic effect vs. C. difficile of 6 to 10 hrs.

Resistance

Fidaxomicin demonstrates no in vitro cross-resistance with other classes of antibacterial drugs.

In vitro studies indicate a low frequency of spontaneous resistance to fidaxomicin in C. difficile (ranging from <1.4 × 10^-9 to 12.8 × 10^-9). A specific mutation (Val-ll43-Gly) in the beta subunit of RNA polymerase is associated with reduced susceptibility to fidaxomicin. This mutation was created in the laboratory and seen during clinical trials in a C. difficile isolate obtained from an adult subject treated with fidaxomicin tablets who had recurrence of CDAD. The fidaxomicin minimum inhibitory concentration (MIC) of the C. difficile isolate from this subject increased from a baseline of 0.06 mcg/mL to 16 mcg/mL at the time of CDAD recurrence.

Interaction With Other Antimicrobials

Fidaxomicin and its main metabolite OP-1118 do not exhibit any antagonistic interaction with other classes of antibacterial drugs. Synergistic interactions of fidaxomicin and OP-1118 have been observed in vitro with rifampin and rifaximin against C. difficile.

Antimicrobial Activity

Fidaxomicin has been shown to be active against most isolates of Clostridioides (formerly Clostridium) difficile, both in vitro and in clinical infections [see Indications and Usage (1)].

Susceptibility Testing

For specific information regarding susceptibility test interpretive criteria, and associated test methods and quality control standards recognized by FDA for this drug, please see: https://www.fda.gov/STIC.

13 NONCLINICAL TOXICOLOGY

13.1 Carcinogenesis, Mutagenesis, Impairment of Fertility

Long-term carcinogenicity studies have not been conducted to evaluate the carcinogenic potential of fidaxomicin.

Neither fidaxomicin nor OP-1118 was mutagenic in the Ames assay. Fidaxomicin was also negative in the rat micronucleus assay. However, fidaxomicin was clastogenic in Chinese hamster ovary cells.

Fidaxomicin did not affect the fertility of male and female rats at intravenous doses of 6.3 mg/kg. The exposure (AUC0-t) was approximately 100 times that in humans.

14 CLINICAL STUDIES

14.1 Clinical Studies of Fidaxomicin Tablets in Adult Patients with CDAD

In two randomized, double-blinded trials, a non-inferiority design was utilized to demonstrate the efficacy of fidaxomicin tablets (200 mg tablets twice daily for 10 days) compared to vancomycin (125 mg four times daily for 10 days) in adults with CDAD.

Enrolled patients were 18 years of age or older and received no more than 24 hours of pretreatment with vancomycin or metronidazole. CDAD was defined by >3 unformed bowel movements (or >200 mL of unformed stool for subjects having rectal collection devices) in the 24 hours before randomization, and presence of either C. difficile toxin A or B in the stool within 48 hours of randomization. Enrolled patients had either no prior CDAD history or only one prior CDAD episode in the past three months. Subjects with life-threatening/fulminant infection, hypotension, septic shock, peritoneal signs, significant dehydration, or toxic megacolon were excluded.

The demographic profile and baseline CDAD characteristics of enrolled subjects were similar in the two trials. Patients had a median age of 64 years, were mainly white (90%), female (58%), and inpatients (63%). The median number of bowel movements per day was 6, and 37% of subjects had severe CDAD (defined as 10 or more unformed bowel movements per day or WBC ≥15,000/mm^3). Diarrhea alone was reported in 45% of patients and 84% of subjects had no prior CDAD episode.

The primary efficacy endpoint was the clinical response rate at the end of treatment, based upon improvement in diarrhea or other symptoms such that, in the investigator's judgment, further CDAD treatment was not needed. An additional efficacy endpoint was sustained clinical response 25 days after the end of treatment. Sustained response was evaluated only for patients who were clinical successes at the end of treatment. Sustained response was defined as clinical response at the end of treatment, and survival without proven or suspected CDAD recurrence through 25 days beyond the end of treatment.

The results for clinical response at the end of treatment in both trials, shown in Table 6, indicate that fidaxomicin tablets is non-inferior to vancomycin based on the 95% confidence interval (CI) lower limit being greater than the non-inferiority margin of -10%.

The results for sustained clinical response at the end of the follow-up period, also shown in Table 6, indicate that fidaxomicin tablets is superior to vancomycin on this endpoint. Since clinical success at the end of treatment and mortality rates were similar across treatment arms (approximately 6% in each group), differences in sustained clinical response were due to lower rates of proven or suspected CDAD during the follow-up period in fidaxomicin tablets patients.

Table 6: Clinical Response Rates at End-of-Treatment and Sustained Response at 25 days Post-Treatment in Adult Patients

 | Clinical Response at End of Treatment |  |  | Sustained Response at 25 days Post- Treatment
 | Fidaxomicin % (N) | Vancomycin % (N) | Difference (95% CI)* | Fidaxomicin % (N) | Vancomycin % (N) | Difference (95% CI)*
Trial 1 | 88% (N=289) | 86% (N=307) | 2.6% (-2.9%, 8.0%) | 70% (N=289) | 57% (N=307) | 12.7% (4.4%, 20.9%)
Trial 2 | 88% (N=253) | 87% (N=256) | 1.0% (-4.8%, 6.8%) | 72% (N=253) | 57% (N=256) | 14.6% (5.8%, 23.3%)

* Confidence interval (CI) was derived using Wilson's score method. Approximately 5%-9% of the data in each trial and treatment arm were missing sustained response information and were imputed using multiple imputation method.

Restriction Endonuclease Analysis (REA) was used to identify C. difficile baseline isolates in the BI group, isolates associated with increasing rates and severity of CDAD in the US in the years prior to the clinical trials. Similar rates of clinical response at the end of treatment and proven or suspected CDAD during the follow-up period were seen in fidaxomicin-treated and vancomycin-treated patients infected with a BI isolate. However, fidaxomicin tablets did not demonstrate superiority in sustained clinical response when compared with vancomycin (Table 7).

Table 7: Sustained Clinical Response at 25 Days after Treatment by C. difficile REA Group at Baseline in Adult Patients

Trial 1
Initial C. difficile Group | Fidaxomicin n/N (%) | Vancomycin n/N (%) | Difference (95% CI)*
BI Isolates | 44/76 (58%) | 52/82 (63%) | -5.5% (-20.3%, 9.5%)
Non-BI Isolates | 105/126 (83%) | 87/131 (66%) | 16.9% (6.3%, 27.0%)
Trial 2
Initial C. difficile Group | Fidaxomicin n/N (%) | Vancomycin n/N (%) | Difference (95% CI)*
BI Isolates | 42/65 (65%) | 31/60 (52%) | 12.9% (-4.2%, 29.2%)
Non-BI Isolates | 109/131 (83%) | 77/121 (64%) | 19.6% (8.7%, 30.0%)

* Interaction test between the effect on sustained response rate and BI versus non-BI isolates using logistic regression (p-values: trial 1: 0.009; trial 2: 0.29). Approximately 25% of the mITT population were missing data for REA group. Confidence intervals (CI) were derived using Wilson's score method.

Pediatric use information is approved for Cubist Pharmaceuticals LLC's DIFICID® (fidaxomicin) tablets. However, due to Cubist Pharmaceuticals LLC's marketing exclusivity rights, this drug product is not labeled with that information.

16 HOW SUPPLIED/STORAGE AND HANDLING

16.1 How Supplied

Fidaxomicin tablets are white to off-white, capsule shape, biconvex film-coated tablet. Engraved “F200” on one side, “APO” on the other side.

Fidaxomicin tablets are supplied as bottles of 20 tablets (NDC 60505-4833-2).

16.2 Storage

Store fidaxomicin tablets at 20°C to 25°C (68°F to 77°F); excursions permitted to 15°C to 30°C (59°F to 86°F). See USP Controlled Room Temperature. Store in the original bottle.

17 PATIENT COUNSELING INFORMATION

Advise the patient to read the FDA-approved patient labeling (Patient Information).

Administration with Food

Inform patients and caregivers that fidaxomicin tablets may be taken with or without food.

Antibacterial Resistance

Patients should be counseled that antibacterial drugs, including fidaxomicin tablets, should only be used to treat bacterial infections. They do not treat viral infections (e.g., the common cold). When fidaxomicin tablets is prescribed to treat a C. difficile infection, patients should be told that, although it is common to feel better early in the course of therapy, the medication should be taken exactly as directed. Skipping doses or not completing the full course of therapy may (1) decrease the effectiveness of the immediate treatment and (2) increase the likelihood that bacteria will develop resistance and will not be treatable by fidaxomicin tablets or other antibacterial drugs in the future.

Rx only

APOTEX INC

FIDAXOMICIN TABLETS

200 mg

Manufactured by:
Apotex Inc.
Toronto, Ontario
Canada M9L 1T9

Manufactured for:
Apotex Corp.
Weston, Florida
33326

Rev. 3

Patient Information

Fidaxomicin (fye dax″ oh mye′ sin) tablets,

for oral use

What You Need to Know About Your Medicine

- Before you take fidaxomicin tablets, be sure you understand what it is for and how to take it.
- If you have questions about fidaxomicin tablets, ask your doctor or pharmacist.
- Remember that your doctor has prescribed fidaxomicin tablets only for you. Never give this medicine to anyone else.
- Keep this Patient Information for fidaxomicin tablets so you can read it again.

What is fidaxomicin tablets?

Fidaxomicin tablets is an antibiotic medicine used to treat an infection called Clostridioides difficile-associated diarrhea (CDAD) in adults. Clostridioides difficile (C-diff) is a bacterium that can cause an infection that can damage your colon and cause stomach pain and severe diarrhea.

- Fidaxomicin tablets are not to be used to treat other types of infections in the body.
- Sometimes infections are caused by viruses rather than bacteria. Antibiotic medicines, including fidaxomicin tablets, do not kill viruses.

It is not known if fidaxomicin tablets are safe and effective in children under 6 months old.

Who should not take fidaxomicin tablets?

Do not take fidaxomicin tablets if you are allergic to fidaxomicin, or any other ingredient in fidaxomicin tablets. See the end of this Patient Information for a complete list of ingredients in fidaxomicin tablets.

What should I tell my doctor before taking fidaxomicin tablets?

Pregnancy

- If you are pregnant or plan to become pregnant, tell your doctor before you take fidaxomicin tablets.
- It is not known if fidaxomicin tablets will harm your baby while you are pregnant.
- If you are pregnant, you and your doctor should decide together if you will take fidaxomicin tablets.

Breastfeeding

- If you are breastfeeding or plan to breastfeed, tell your doctor before you take fidaxomicin tablets.
- It is not known if fidaxomicin passes into breast milk.
- If you are breastfeeding, you and your doctor should decide together if you will take fidaxomicin tablets.

Other Medicines

- Tell your doctor about all of the medicines you take, including prescription and over-the-counter medicines, vitamins, and herbal and dietary supplements.
- Know the medicines you take. Keep a list of your medicines to show your doctor and pharmacist when you get a new medicine.

Allergic Reactions

- See “Who should not take fidaxomicin tablets?”
- If you are allergic to other kinds of antibiotics called macrolides (for example: azithromycin (Zithromax) or clarithromycin (Biaxin)) or any other ingredient in fidaxomicin tablets, tell your doctor. See the end of this Patient Information for a complete list of ingredients in fidaxomicin tablets.

How do I take fidaxomicin tablets?

- Take fidaxomicin tablets exactly as prescribed by your doctor.
- Take fidaxomicin tablets twice a day (approximately every 12 hours). For example, if you take your first dose at 8:00 a.m. you should take your second dose at 8:00 p.m.
- You can take fidaxomicin tablets with or without food.

- Do not skip any doses or stop taking fidaxomicin tablets until you finish your prescribed treatment, even if you begin to feel better, unless you have a serious allergic reaction (see “What are the possible side effects of fidaxomicin tablets?”).

This will lower the chance that the bacteria will become resistant to fidaxomicin tablets. If this happens, fidaxomicin tablets and other antibiotic medicines may not work in the future.

What are the possible side effects of fidaxomicin tablets?

Fidaxomicin tablets can cause serious side effects, including:

- Allergic reaction. If you get a severe allergic reaction while taking fidaxomicin tablets, including problems breathing or shortness of breath, rash, itching or hives, or swelling of the mouth, throat, or face, stop taking fidaxomicin tablets and get emergency medical help right away.

Common side effects of fidaxomicin tablets include:

The most common side effects of fidaxomicin tablets in adults include:

- nausea
- bleeding in the stomach or intestines
- vomiting
- low red blood cell count (anemia)
- stomach pain
- low white blood cell count (neutropenia)

Other less common side effects of fidaxomicin tablets may include:

- swelling of any body part (such as your face, lips, tongue or around your eyes)
- passing gas
- itching
- intestinal blockage
- hives
- serious bowel inflammation (toxic megacolon)
- bloating
- low platelet count (important for clotting and to control bleeding)
- stomach tenderness
- high levels of acid in your blood (metabolic acidosis)
- heartburn
- problems swallowing
- high blood sugar (hyperglycemia)
- abnormal liver tests
- low levels of blood bicarbonate

If you have any side effect that bothers you or does not go away, tell your doctor.

There may be other side effects to fidaxomicin tablets that are not listed. Call your doctor for medical advice about side effects. You may report side effects to FDA at 1-800-FDA-1088.

How should I store fidaxomicin tablets?

- Store fidaxomicin tablets at room temperature between 68°F to 77°F (20°C to 25°C).
- Keep fidaxomicin tablets in its original bottle until you are ready to take it.

Keep fidaxomicin tablets and all medicines out of the reach of children.

General information about the safe and effective use of fidaxomicin tablets.

Medicines are sometimes prescribed for purposes other than those listed in the Patient Information. Do not take fidaxomicin tablets for a condition for which it was not prescribed. Do not give fidaxomicin tablets to other people, even if they have the same symptoms that you have. It may harm them. You can ask your pharmacist or doctor for information about fidaxomicin tablets that is written for health professionals.

What if I have questions?

- Call your doctor.
- Call Apotex Corp, the company that makes fidaxomicin tablets at 1-800-706-5575.
- Go to the website – www.apotex.com.
- You can also find the full prescribing information written for doctors at www.apotex.com

What are the ingredients in fidaxomicin tablets?

- Active ingredient: fidaxomicin.
- Inactive ingredients: butylated hydroxytoluene, hydroxypropyl cellulose, magnesium stearate, microcrystalline cellulose, polyethylene glycol, polyvinyl alcohol, pregelatinized starch, sodium starch glycolate, talc, and titanium dioxide.

Pediatric use information is approved for Cubist Pharmaceuticals LLC's DIFICID® (fidaxomicin) tablets. However, due to Cubist Pharmaceuticals LLC's marketing exclusivity rights, this drug product is not labeled with that information.

All registered trademarks in this document are the property of their respective owners.

This Patient Information has been approved by the U.S. Food and Drug Administration.

Rx only

APOTEX INC

FIDAXOMICIN TABLETS

200 mg

Manufactured by:
Apotex Inc.
Toronto, Ontario
Canada M9L 1T9

Manufactured for:
Apotex Corp.
Weston, Florida
33326

Revised: May 2025

Rev. 3

PACKAGE LABEL PRINCIPAL DISPLAY PANEL - Bottle Label

NDC 60505-4833-2

Fidaxomicin Tablets

200 mg

Bottle of 20 Tablets

Rx only

PACKAGE LABEL PRINCIPAL DISPLAY PANEL - Carton Label

NDC 60505-4833-2

Fidaxomicin Tablets

200 mg

Bottle of 20 Tablets

Rx only